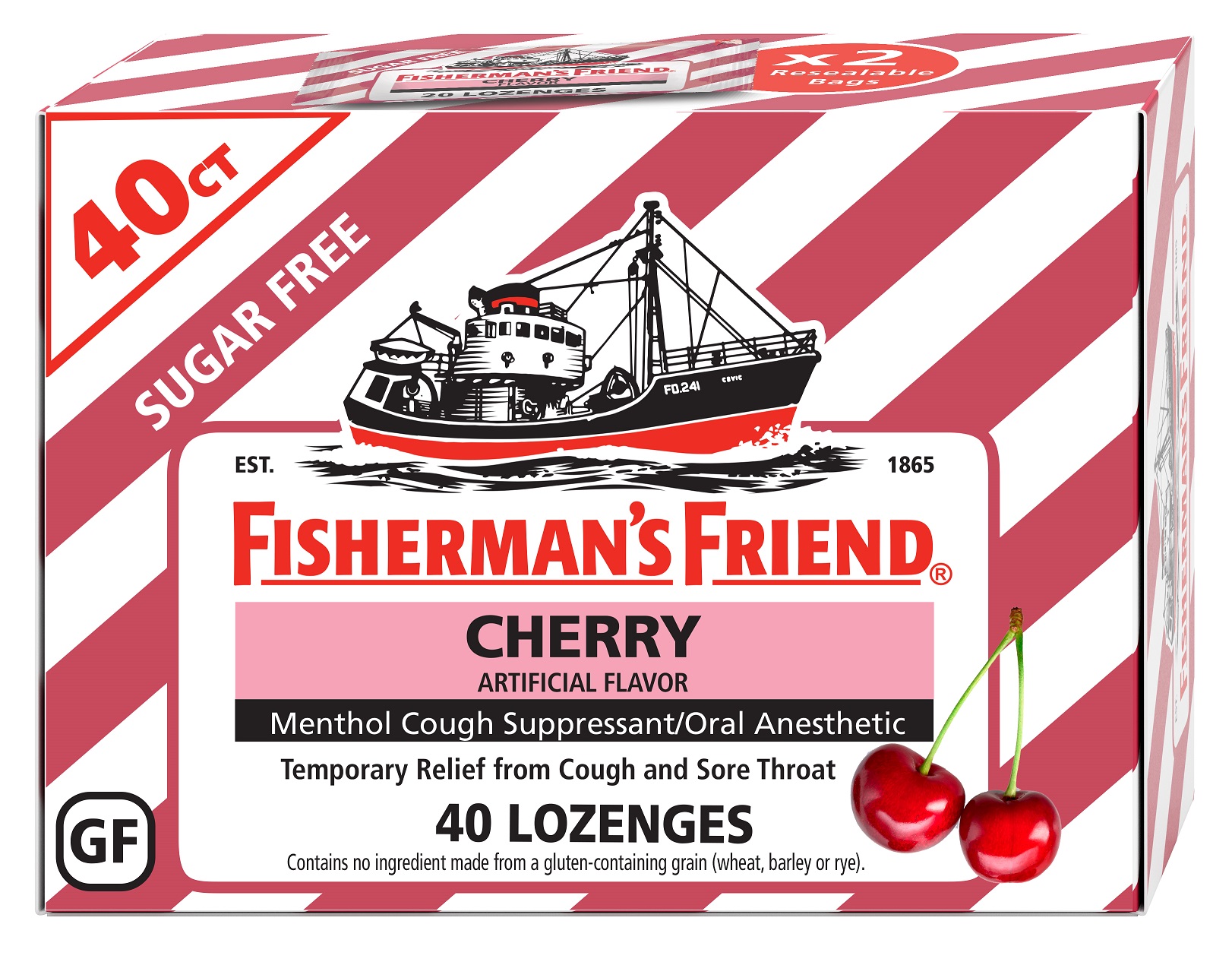 DRUG LABEL: Sugar Free Cherry Fishermans Friend Menthol Cough Suppressant
NDC: 55711-070 | Form: LOZENGE
Manufacturer: Lofthouse of Fleetwood, Ltd.
Category: otc | Type: HUMAN OTC DRUG LABEL
Date: 20251014

ACTIVE INGREDIENTS: MENTHOL 6.9 mg/1 1
INACTIVE INGREDIENTS: MAGNESIUM STEARATE; SUCRALOSE; ACESULFAME POTASSIUM; SORBITOL

Cherry 2 bags of 20 lozenges

Active ingredient (in each lozenge)

Menthol 6.9 mg

Purpose

Cough suppressant/oral anesthetic

Uses

temporarily relieves

- occasional minor sore throat
- cough due to minor throat and bronchial irritation occurring with the common cold or inhaled irritants

Warnings

Sore throat warning: Severe or persistent sore throat or sore throat that occurs with high fever, headache, nausea, and vomiting may be serious. Ask a doctor right away. Do not use more than 2 days or give to children under 2 years of age unless directed by a doctor.

Ask a doctor before use if you have

- cough that occurs with too much phlegm (mucus)
- a persistent or chronic cough that lasts such as occurs with smoking, asthma, or emphysema

When using this product

do not use more than directed

Stop use and ask a doctor if

- cough lasts more than 7 days, comes back, or occurs with fever, rash, or headache that lasts. These could be signs of a serious condition.
- Sore throat is severe, lasts more than 2 days, is accompanied or followed by fever, headache, rash, swelling, nausea, or vomiting.

If pregnant or breast-feeding

ask a health professional before use.

Keep out of reach of children.

Directions

- adults and children 2 years of age and over: allow 1 lozenge to dissolve slowly in the mouth
- repeat every 2 hours as needed or as directed by a doctor
- children under 2 years of age: ask a doctor

Inactive ingredients

acesulfame K, cherry flavour (including elderberry juice concentrate), herbal flavour, magnesium stearate, sorbitol, sucralose

PACKAGE LABEL

FISHERMAN'S FRIEND®
CHERRY

Menthol Cough Suppressant Lozenges

2 Bags of 20 Lozenges

Cough Suppressant/Oral Anesthetic

2 PACK

Manufactured by: Lofthouse of Fleetwood Ltd., Lancs, England

Distributed by: Greenwood Brands, LLC. Buffalo-Niagara, NY 14225

ffinfo@greenwoodg.com